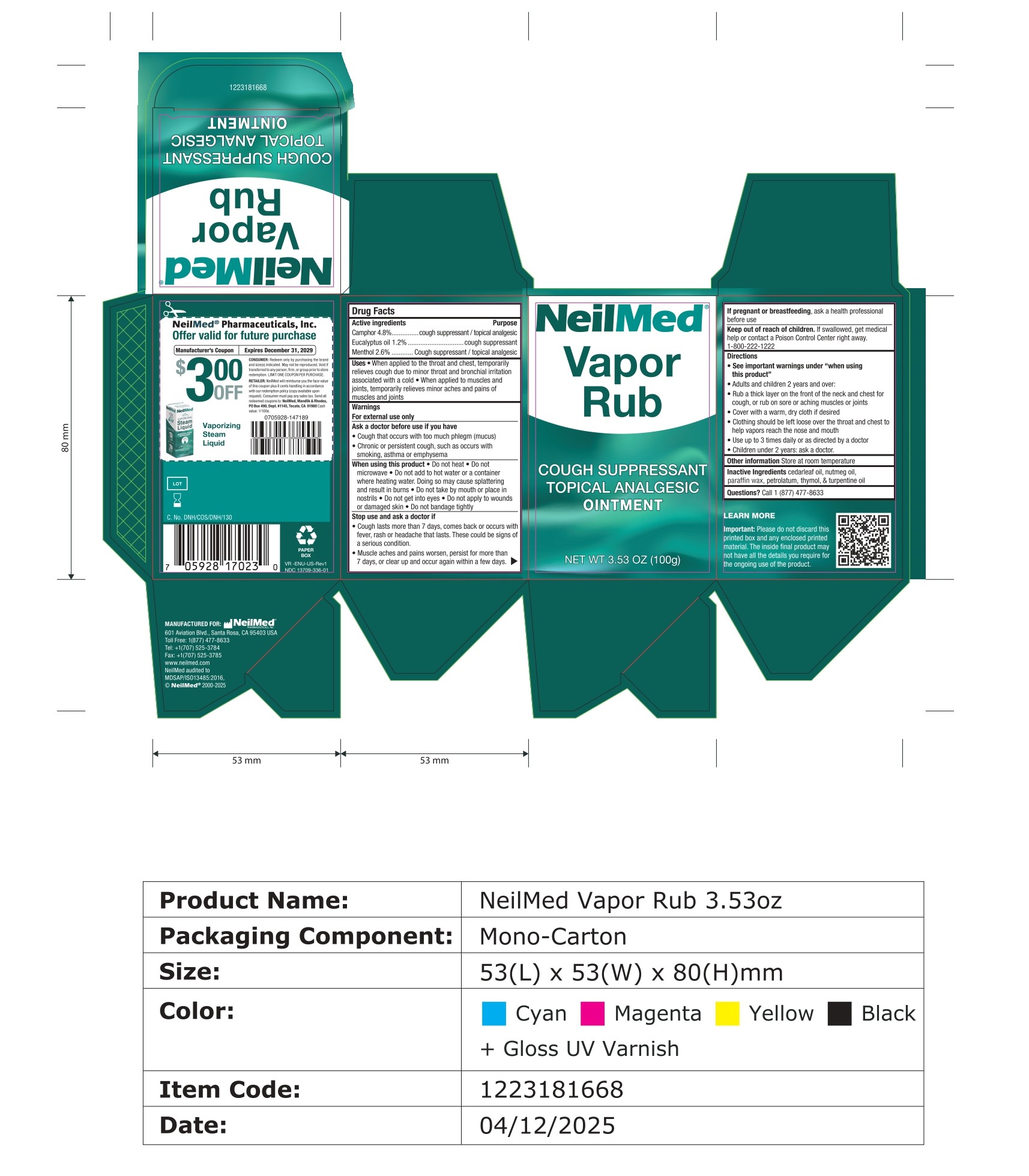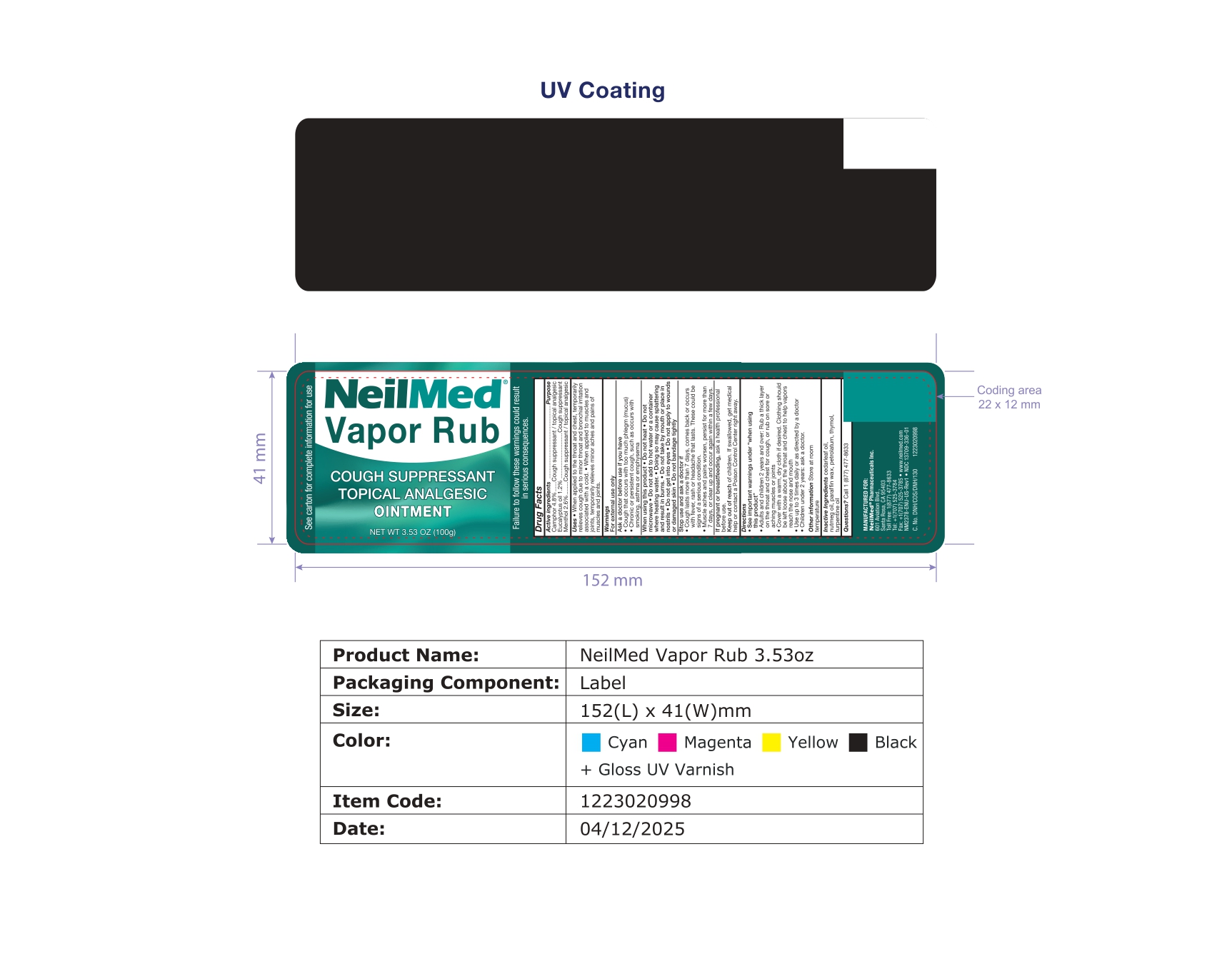 DRUG LABEL: Vapor Rub
NDC: 13709-336 | Form: OINTMENT
Manufacturer: Neilmed Pharmaceuticals Inc.
Category: otc | Type: HUMAN OTC DRUG LABEL
Date: 20251212

ACTIVE INGREDIENTS: MENTHOL 0.026 g/1 g; CAMPHOR (SYNTHETIC) 0.048 g/1 g; EUCALYPTUS OIL 0.012 g/1 g
INACTIVE INGREDIENTS: PARAFFIN; TURPENTINE OIL; CEDAR LEAF OIL; THYMOL; NUTMEG OIL; PETROLATUM

Vapor Rub

Drug Facts

Active ingredients

Camphor 4.8%

Eucalyptus oil 1.2%

Menthol 2.6%

Purpose

Cough suppressant / topical analgesic

Cough suppressant

Cough suppressant / topical analgesic

Uses

- When applied to the throat and chest, temporarily relieves cough due to minor throat and bronchial irritation associated with a cold
- When applied to muscles and joints, temporarily relieves minor aches and pains of muscles and joints

Warnings

For external use only

Ask a doctor before use if you have

- Cough that occurs with too much phlegm (mucus)
- Chronic or persistent cough, such as occurs with smoking, asthma or emphysema

When using this product

- Do not heat • Do not microwave
- Do not add to hot water or an container where heating water.
- May cause splattering and result in burns
- Do not take by mouth or place in nostrils
- Do not get into eyes
- Do not apply to wounds or damaged skin
- Do not bandage tightly

Stop use and ask a doctor if

- Cough lasts more than 5 days, comes back or occurs with fever, rash or headache that lasts. These could be signs of a serious condition.
- Muscle aches and pains worsen, persist for more than 5 days, or clear up and occur again within a few days.

If pregnant or breastfeeding,

ask a health professional before use

Keep out of reach of children.

If swallowed, get medical help or contact a Poison Control Center right away. 1-800-222-1222

Directions

- See important warnings under “when using this product”
- Adults and children 2 years and over:
- Rub a thick layer on the front of the neck and chest for cough, or rub on sore or aching muscles or joints
- Cover with a warm, dry cloth if desired
- Clothing should be left loose over the throat and chest to help vapors reach the nose and mouth
- Use up to 3 times daily or as directed by a doctor
- Children under 2 years: ask a doctor.

Other Information

Store at room temperature

Inactive Ingredients

Cedarleaf oil, Nutmeg oil, Paraffin Wax, Petrolatum, Thymol, & Turpentine oil

Questions?

Call 1 (877) 477-8633

Important:

Please do not discard this printed box and any enclosed printed material. The inside final product may not have all the details you require for the ongoing use of the product.